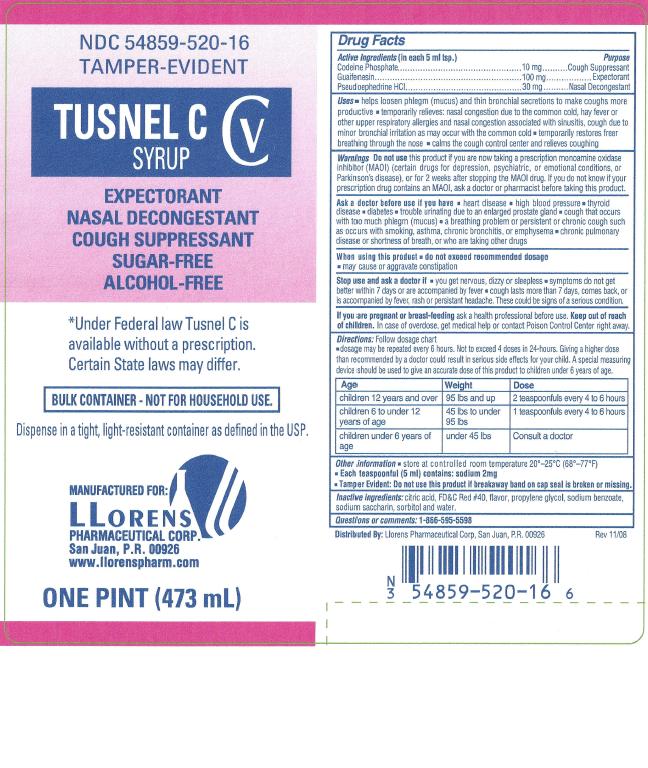 DRUG LABEL: Tusnel
NDC: 54859-520 | Form: LIQUID
Manufacturer: Llorens Pharmaceutical International Division
Category: otc | Type: HUMAN OTC DRUG LABEL
Date: 20251231
DEA Schedule: CIII

ACTIVE INGREDIENTS: CODEINE PHOSPHATE 10 mg/5 mL; GUAIFENESIN 100 mg/5 mL; PSEUDOEPHEDRINE HYDROCHLORIDE 30 mg/5 mL
INACTIVE INGREDIENTS: FD&C RED NO. 40; CITRIC ACID MONOHYDRATE; SODIUM BENZOATE; SACCHARIN SODIUM; SORBITOL; PROPYLENE GLYCOL; WATER

Llorens- Tusnel CV 520

Active Ingredients(in each 5 ml tsp.) Purpose

Codeine Phosphate ................................................. 10 mg .......... Cough Suppressant

Guaifenesin .......................................................... 100 mg .................. Expectorant

Pseudoephedrine HCl ............................................. 30 mg .......... Nasal Decongestant

Uses

- helps loosen phlegm (mucus) and thin bronchial secretions to make coughs more productive
- temporarily relieves: nasal congestion due to the common cold, hay fever or other upper respiratory allergies and nasal congestion associated with sinusitis, cough due to minor bronchial irritation as may occur with the common cold
- temporarily restores freer breathing through the nose
- calms the cough control center and relieves coughing

Warnings

Do not use if you are now taking a prescription monoamine oxidase
inhibitor (MAOI) (certain drugs for depression, psychiatric, or emotional
conditions, or Parkinson’s disease), or for 2 weeks after stopping the
MAOI drug. If you do not know if your prescription drug contains an
MAOI, ask a doctor or pharmacist before taking this product.

When using this product
do nol exceed recommended dosage
• may cause or aggravate constipation

Ask a doctor before use if you have

- heart disease
- high blood pressure
- thyroid disease
- diabetes
- trouble urinating due to an enlarged prostate gland
- cough that occurs with too much phlegm (mucus)
- a breathing problem or persistent or chronic cough such as occurs with smoking, asthma, chronic bronchitis, or emphysema. chronic pulmonary disease or shortness of breath, or who are taking other drugs

Stop use and ask a doctor if

- you get nervous, dizzy or sleepless. symptoms do not get better within 7 days or are accompanied by fever. cough lasts more than 7 days, comes back, or is accompanied by fever, rash or persistant headache. These could be signs of a serious condition.

Keep out of reach of children.In case of overdose, get medical helpor contact a Poison Control Center right away.

PREGNANCY OR BREAST FEEDING

If pregnant or breast-feeding, ask a health professional before use.

DOSAGE AND ADMINISTRATION

Directions: Follow dosage chartDosage may be repeated every 6 hours. Not to exceed 4 doses in 24-hours. Giving a higher dose
than recommended by a doctor could result in serious side effects for your child. A special measuring
device should be used to give an accurate dose of this product to children under 6 years of age.

Age | Weight | Dose
children 12 years of age and over | 95 lbs and up | Take 2 teaspoonfuls (10 mL) every 6 hours
Children 6 to under 12 years of age | 45 lbs to under 95 lbs | Take 1 teaspoonful (5mL) every 6 hours
Children under 6 years of age | under 45 lbs | ask a doctor

Other information

- store at controlled room temperature 20°- 25°C (68°- 77°F)
- Each teaspoonful (5 ml) contains: sodium 2mg

- Tamper evident by imprinted heat seal under cap. Do not use if there is evidence of tampering.

Inactive ingredientsaspartame, citric acid, glycerine, methylparaben,
natural and artificial flavors, potassium citrate, potassium sorbate,
propylene glycol, propylparaben, purified water.

Questions or Comments?1-866-595-5598